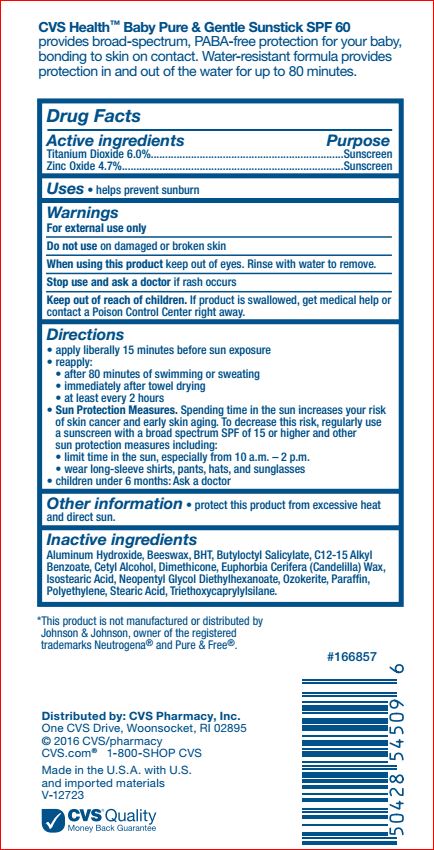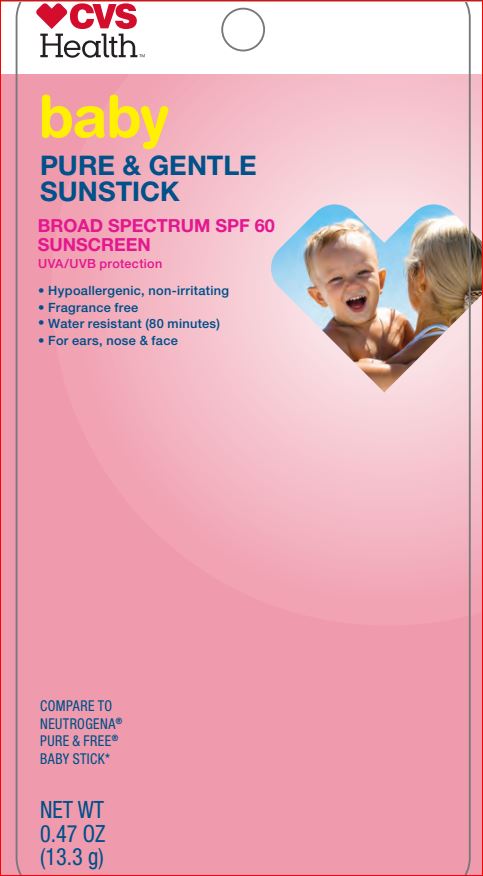 DRUG LABEL: Baby Pure and Gentle SPF 60 Sunscreen
NDC: 69842-333 | Form: STICK
Manufacturer: CVS
Category: otc | Type: HUMAN OTC DRUG LABEL
Date: 20180423

ACTIVE INGREDIENTS: Titanium Dioxide 6 g/100 g; Zinc Oxide 4.7 g/100 g
INACTIVE INGREDIENTS: Aluminum Hydroxide; YELLOW WAX; BUTYLATED HYDROXYTOLUENE; Butyloctyl Salicylate; ALKYL (C12-15) BENZOATE; Cetyl Alcohol; Dimethicone; CANDELILLA WAX; Isostearic Acid; Neopentyl Glycol Diethylhexanoate; CERESIN; Paraffin; HIGH DENSITY POLYETHYLENE; Stearic Acid; Triethoxycaprylylsilane

CVS Health
Drug Facts

Active ingredients Purpose

Titanium Dioxide - 6.00% Sunscreen
Zinc Oxide - 4.70% Sunscreen

Uses

helps prevent sunburn

Warnings For external use only

Do not use on damage or broken skin

When using this product keep out of eyes. Rinse with water to remove.

Stop use and ask a doctor if rash occurs

KEEP OUT OF REACH OF CHILDREN

Keep out of reach of the children. If swallowed, get medical help or contact a Poison Control Center right away

Directions

• apply liberally 15 minutes before sun exposure
• reapply:
- after 80 minutes of swimming or sweating
- immediately after towel drying
- at least every 2 hours
• Sun Protection Measures. Spending time in the sun increases your risk of skin cancer and early skin aging. To decrease this risk, regularly use a sunscreen SPF of 15 or higher and other sun protection measures including:
- limit time in the sun, especially from 10 a.m. – 2 p.m.
- wear long sleeve shirts, pants, hats, and sunglasses
• children under 6 month: Ask a doctor

Inactive ingredients

Aluminum Hydroxide, Beeswax, BHT, Butyloctyl Salicylate, C12-15 Alkyl Benzoate, Cetyl Alcohol, Dimethicone, Euphorbia Cerifera (Candelilla) Wax, Isostearic Acid, Neopentyl Glycol Diethylhexanoate, Ozokerite, Paraffin, Polyethylene, Stearic Acid, Triethoxycaprylylsilane

Other Information

• protect this product from excessive heat and direct sun